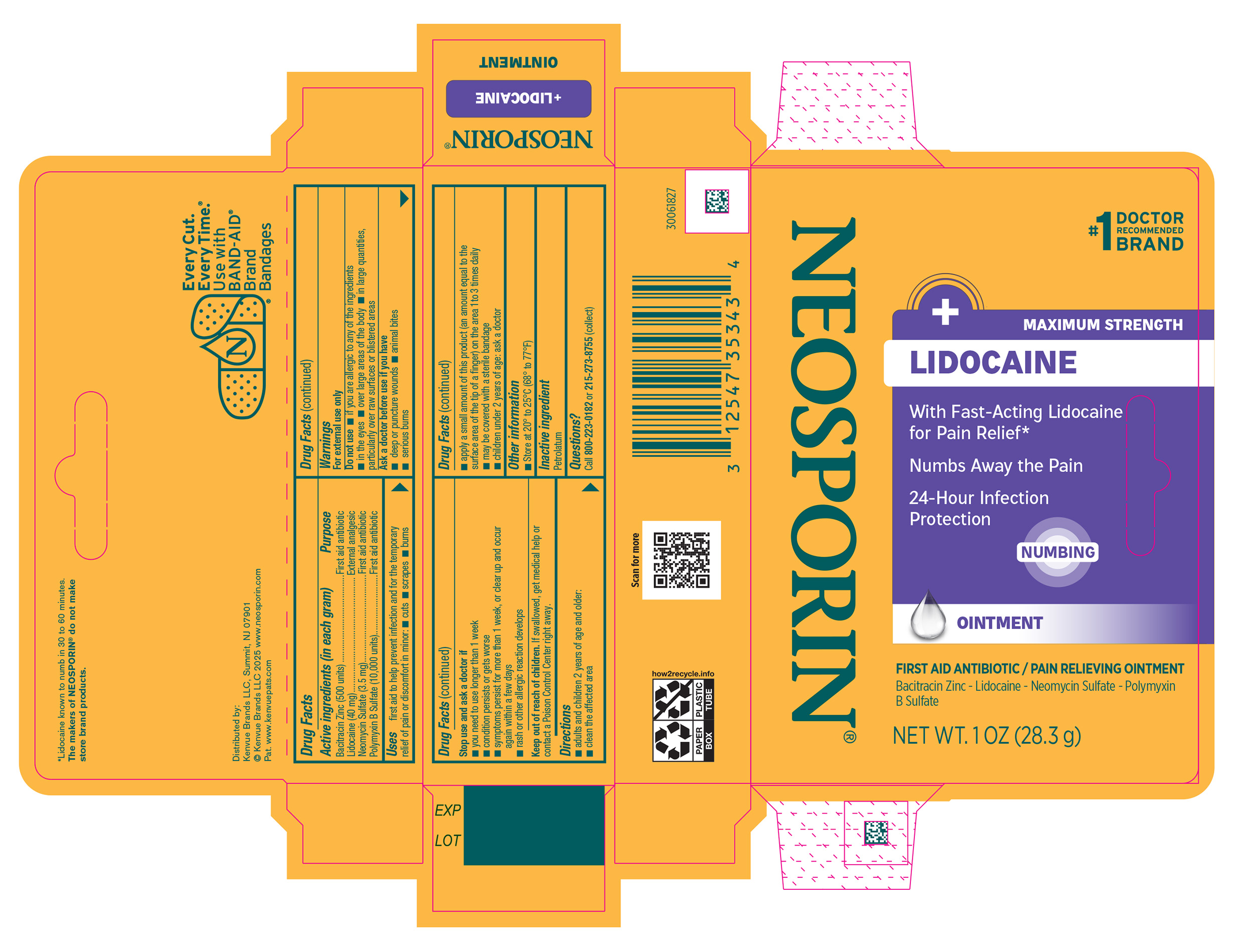 DRUG LABEL: Neosporin Plus Lidocaine
NDC: 69968-0731 | Form: OINTMENT
Manufacturer: Kenvue Brands LLC
Category: otc | Type: HUMAN OTC DRUG LABEL
Date: 20251124

ACTIVE INGREDIENTS: LIDOCAINE 40 mg/1 g; BACITRACIN ZINC 500 [iU]/1 g; NEOMYCIN SULFATE 3.5 mg/1 g; POLYMYXIN B SULFATE 10000 [iU]/1 g
INACTIVE INGREDIENTS: PETROLATUM

Neosporin + Lidocaine

Drug Facts

ACTIVE INGREDIENT

Active ingredients (in each gram) | Purpose
Bacitracin Zinc (500 units) | First aid antibiotic
Lidocaine (40 mg) | External analgesic
Neomycin Sulfate (3.5 mg) | First aid antibiotic
Polymyxin B sulfate (10,000 units) | First aid antibiotic

Uses

first aid to help prevent infection and for the temporary relief of pain or discomfort in minor:

- cuts
- scrapes
- burns

Warnings

For external use only

Do not use

- if you are allergic to any of the ingredients
- in the eyes
- over large areas of the body
- in large quantities, particularly over raw surfaces or blistered areas

Ask a doctor before use if you have

- deep or puncture wounds
- animal bites
- serious burns

Stop use and ask a doctor if

- you need to use longer than 1 week
- condition persists or gets worse
- symptoms persist for more than 1 week, or clear up and occur again within a few days
- rash or other allergic reaction develops

Keep out of reach of children. If swallowed, get medical help or contact a Poison Control Centre right away.

Directions

- adults and children 2 years of age and older:
  - clean the affected area
  - apply a small amount of this product (an amount equal to the surface area of the tip of a finger) on the area 1 to 3 times daily
  - may be covered with a sterile bandage
- children under 2 years of age: ask a doctor

Other information

- store at 20° to 25°C (68° to 77°F)

Inactive ingredient

Petrolatum

Questions?

Call 800-223-0182 or 215-273-8755 (collect)

Distributed by:
Kenvue Brands LLC
Summit, NJ 07901

PRINCIPAL DISPLAY PANEL - 28.3 g Tube Carton

#1

DOCTOR

RECOMMENDED

BRAND

NEOSPORIN®

+ MAXIMUM STRENGTH

LIDOCAINE

With Fast-Acting Lidocaine

For Pain Relief*

Numbs Away the Pain

24-Hour Infection

Protection

NUMBING

OINTMENT

FIRST AID ANTIBIOTIC / PAIN RELIEVING OINTMENT

Bacitracin Zinc – Lidocaine – Neomycin Sulfate – Polymyxin

B Sulfate

NET WT. 1 OZ (28.3 g)